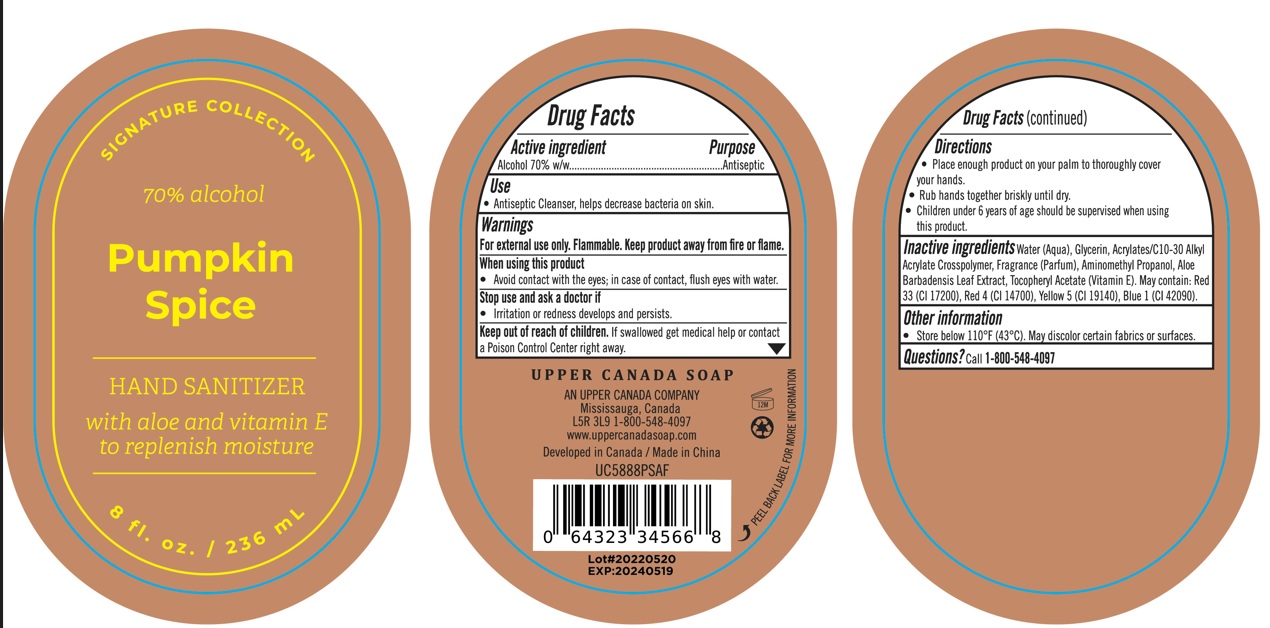 DRUG LABEL: At Home Signature Collection Hand Sanitizer
NDC: 56136-040 | Form: GEL
Manufacturer: Ganzhou Olivee Cosmetic Co., Ltd.
Category: otc | Type: HUMAN OTC DRUG LABEL
Date: 20220617

ACTIVE INGREDIENTS: ALCOHOL 700 mg/1 mL
INACTIVE INGREDIENTS: WATER; GLYCERIN; CARBOMER INTERPOLYMER TYPE A (ALLYL SUCROSE CROSSLINKED); AMINOMETHYLPROPANOL; ALOE VERA LEAF; .ALPHA.-TOCOPHEROL ACETATE, DL-; D&C RED NO. 33; FD&C RED NO. 4; FD&C YELLOW NO. 5; FD&C BLUE NO. 1

Drug Facts

Active ingredient

Alcohol 70% w/w

Purpose

Antiseptic

Use

Antiseptic Cleanser, helps decrease bacteria on skin.

Warnings

For external use only. Flammable. Keep product away from fire or flame.

When using this product

Avoid contact with the eyes; in case of contact, flush eyes with water.

Stop use and ask a doctor if

Irritation or redness develops and persists.

Keep out of reach of children.

If swallowed, get medical help or contact a Poison Control Center right away.

Directions

- Place enough product on your palm to thoroughly cover your hands
- Rub hands together briskly until dry
- Children under 6 years of age should be supervised when using this product

Inactive ingredients

Water (Aqua), Glycerin, Acrylates/C10-30 Alkyl Acrylate Crosspolymer, Fragrance (Parfum), Aminomethyl Propanol, Aloe Barbadensis Leaf Extract, Tocopheryl Acetate. May contain: Red 33 (CI 17200), Red 4 (CI 14700), Yellow 5 (CI 19140), Blue 1 (CI 42090).

Other information

Store below 110°F (43°C). May discolor certain fabrics or surfaces.

Questions?

Call 1-800-548-4097